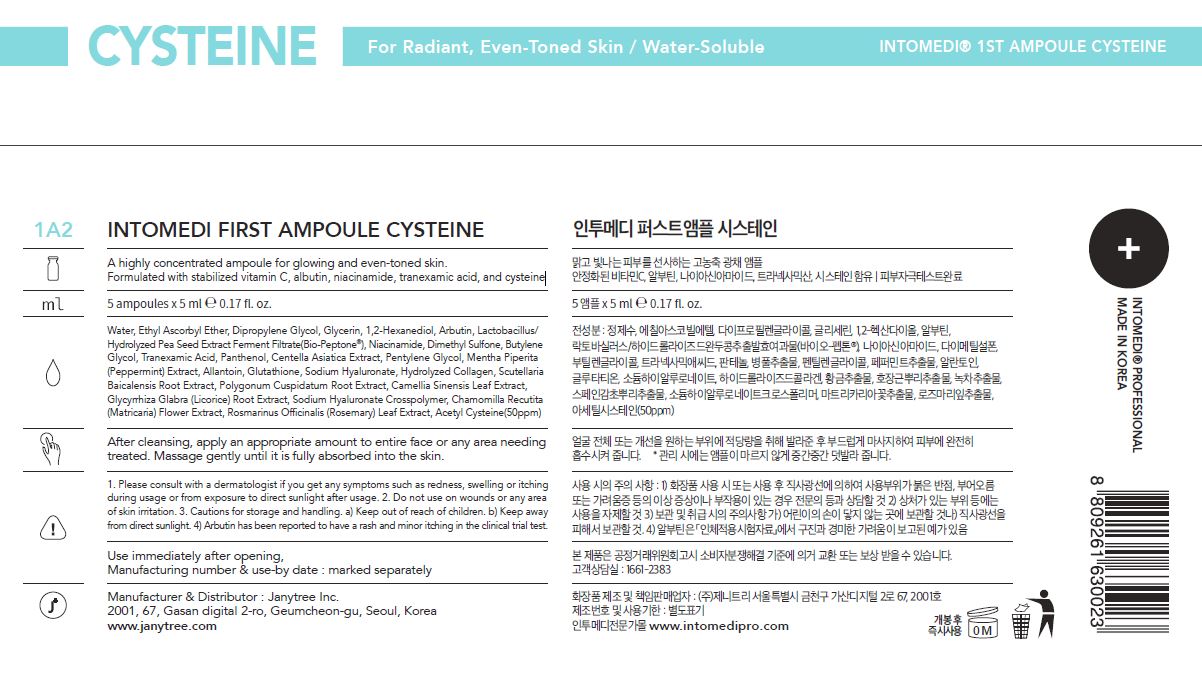 DRUG LABEL: INTOMEDI FIRST AMPOULE CYSTEINE
NDC: 82879-0004 | Form: LIQUID
Manufacturer: Janytree Inc.
Category: otc | Type: HUMAN OTC DRUG LABEL
Date: 20220712

ACTIVE INGREDIENTS: NIACINAMIDE 2 g/100 mL
INACTIVE INGREDIENTS: BUTYLENE GLYCOL; WATER; GLYCERIN

INACTIVE INGREDIENTS

Water, Ethyl Ascorbyl Ether, Dipropylene Glycol, Glycerin, 1,2-Hexanediol, Arbutin, Lactobacillus/
Hydrolyzed Pea Seed Extract Ferment Filtrate(Bio-Peptone®), Dimethyl Sulfone, Butylene
Glycol, Tranexamic Acid, Panthenol, Centella Asiatica Extract, Pentylene Glycol, Mentha Piperita
(Peppermint) Extract, Allantoin, Glutathione, Sodium Hyaluronate, Hydrolyzed Collagen, Scutellaria
Baicalensis Root Extract, Polygonum Cuspidatum Root Extract, Camellia Sinensis Leaf Extract,
Glycyrrhiza Glabra (Licorice) Root Extract, Sodium Hyaluronate Crosspolymer, Chamomilla Recutita
(Matricaria) Flower Extract, Rosmarinus Officinalis (Rosemary) Leaf Extract, Acetyl Cysteine(50ppm)

ACTIVE INGREDIENTS

niacinamide

PURPOSE

A highly concentrated ampoule for glowing and even-toned skin.
Formulated with stabilized vitamin C, albutin, niacinamide, tranexamic acid, and cysteine

WARNINGS

For external use only When using this product
■ If following abnormal symptoms occurs after using the product, stop using the product and consult with a skin specialist. Symptoms : Red specks, swelling, itching
■ Do not use on the skin parts affected by wound, eczema, or dermatitis.
Keep out of reach of children.
■ If swallowed, get a medical help or contact a person in control center immediately.
■ Avoid contact with eyes.

KEEP OUT OF REACH OF CHILDREN

If swallowed, get a medical help or contact a person in control center immediately.

INDICATIONS AND USAGE

apply a proper amount to the skin, and massage gently until fully absorbed

DOSAGE AND ADMINISTRATION

for external use only